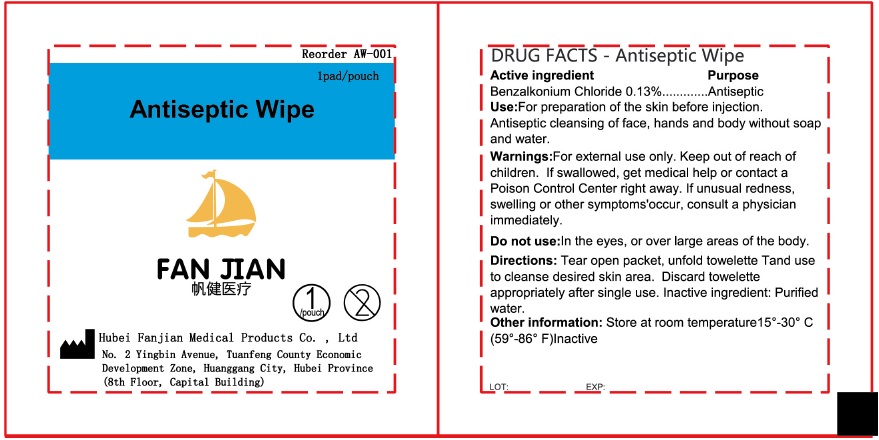 DRUG LABEL: Antiseptic Wipe
NDC: 83165-002 | Form: CLOTH
Manufacturer: Hubei Fanjian Medical Product Co.,Ltd
Category: otc | Type: HUMAN OTC DRUG LABEL
Date: 20231110

ACTIVE INGREDIENTS: BENZALKONIUM CHLORIDE 1.3 mg/1 mL
INACTIVE INGREDIENTS: WATER

Antiseptic Wipe

Active ingredient

Benzalkonium Chloride 0.13%

Purpose

First Aid Antiseptic

Use:

For preparation of the skin before injection. Antiseptic cleansing of face, hands and body without soap and water.

Warnings:

For external use only.

Keep out of reach of children.

If swallowed, get medical help or contact a Poison Control Center right away. If unusual redness, swelling or other symptoms'occur, consult a physician immediately.

Do not use:

In the eyes, or over large areas of the body.

Directions:

Tear open packet, unfold towelette Tand use to cleanse desired skin area. Discard towelette appropriately after single use.

Other information:

Store at room temperature15°-30° C (59°-86° F)

Inactive ingredients

Purified water.